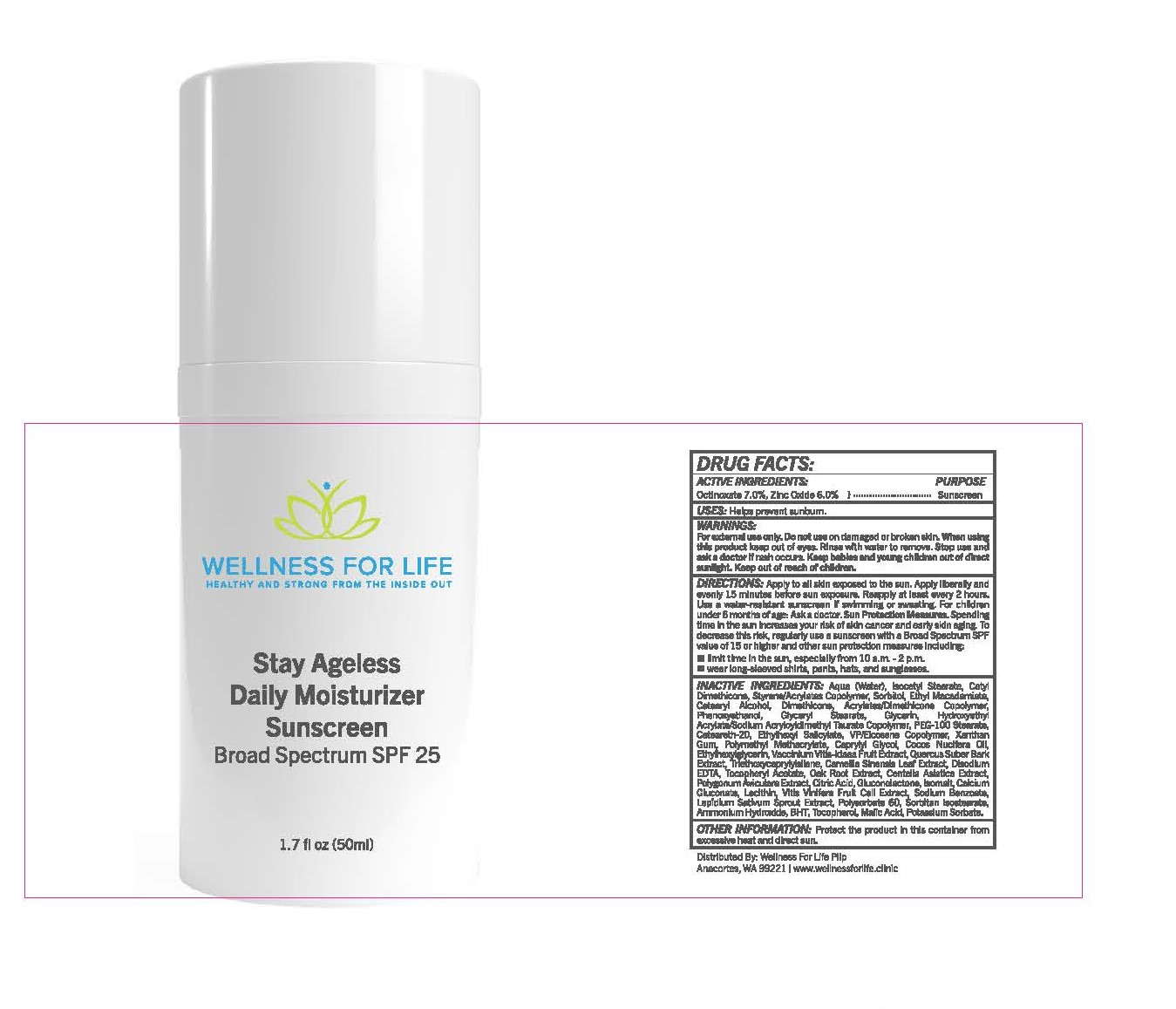 DRUG LABEL: Stay Ageless Daily Moisturizing Sunscreen Broad Spectrum SPF 25
NDC: 82921-2650 | Form: LOTION
Manufacturer: WELLNESS FOR LIFE PLLP
Category: otc | Type: HUMAN OTC DRUG LABEL
Date: 20240116

ACTIVE INGREDIENTS: OCTINOXATE 7 g/100 mL; ZINC OXIDE 6 g/100 mL
INACTIVE INGREDIENTS: WATER; ISOCETYL STEARATE; SORBITOL; ETHYL MACADAMIATE; CETOSTEARYL ALCOHOL; DIMETHICONE; PHENOXYETHANOL; GLYCERYL MONOSTEARATE; GLYCERIN; HYDROXYETHYL ACRYLATE/SODIUM ACRYLOYLDIMETHYL TAURATE COPOLYMER (100000 MPA.S AT 1.5%); PEG-100 STEARATE; POLYOXYL 20 CETOSTEARYL ETHER; OCTISALATE; XANTHAN GUM; POLY(METHYL METHACRYLATE; 450000 MW); CAPRYLYL GLYCOL; ETHYLHEXYLGLYCERIN; LINGONBERRY; QUERCUS SUBER BARK; TRIETHOXYCAPRYLYLSILANE; GREEN TEA LEAF; EDETATE DISODIUM ANHYDROUS; .ALPHA.-TOCOPHEROL ACETATE; CENTELLA ASIATICA WHOLE; POLYGONUM AVICULARE TOP; CITRIC ACID MONOHYDRATE; GLUCONOLACTONE; ISOMALT; CALCIUM GLUCONATE; SODIUM BENZOATE; GARDEN CRESS SPROUT

Stay Ageless Daily Moisturizing Sunscreen Broad Spectrum SPF 25

Drug Facts

ACTIVE INGREDIENT

Active Ingredients | Purpose
Octinoxate (7.0%) | Sunscreen
Zinc Oxide (6.0%) | Sunscreen

Uses

- Helps prevent sunburn
- If used as directed with other sun protection measures (see Directions), decreases the risk of skin cancer and early skin aging caused by the sun

Warnings

For external use only

- Do not use on damaged or broken skin
- When using this product keep out of eyes
- Rinse with water to remove
- Stop use and ask a doctor if rash occurs

- Keep out of reach of children. If swallowed, get medical help or contact a Poison Control Center right away.

Directions

- Apply to all skin exposed to the sun
- Apply liberally 15 minutes before sun exposure
- Reapply:
  - After 2 hours of swimming or sweating
  - Immediately after towel drying
  - At least every 2 hours
- Sun Protection Measures. Spending time in the sun increases your risk of skin and early skin aging. To decrease this risk, regularly use a sunscreen with a broad spectrum SPF of 15 or higher and other sun protection measures including:
  - Limit time in the sun, especially from 10 a.m. - 2 p.m.
  - Wear long-sleeved shirts, pants, hats and sunglasses
- Children under 6 months: Ask a doctor

Inactive Ingredients

Water, Isocetyl Stearate, Cetyl Dimethicone, Styrene/Acrylates Copolymer, Sorbitol, Ethyl Macadamiate, Cetearyl Alcohol, Dimethicone, Acrylates/Dimethicone Copolymer, Phenoxyethanol, Glyceryl Stearate, Glycerin, Hydroxyethyl Acrylate/Sodium Acryloyldimethyl Taurate Copolymer, PEG-100 Stearate, Ceteareth-20, Ethylhexyl Salicylate, VP/Eicosene Copolymer, Xanthan Gum, Polymethyl Methacrylate, Caprylyl Glycol, Coconut (Cocos Nucifera) Oil, Ethylhexylglycerin, Vaccinium Vitis-Idaea Fruit Extract, Cork Oak (Quercus Suber) Bark Extract, Triethoxycaprylylsilane, Tea Plant (Camellia Sinensis) Leaf Extract, Disodium EDTA, Tocopheryl Acetate, Oak (Quercus) Root Extract, Gotu Kola (Centella Asiatica) Extract, Knotweed (Polygonum Aviculare) Extract, Citric Acid, Gluconolactone, Isomalt, Calcium Gluconate, Lecithin, Grape (Vitis Vinifera) Fruit Cell Extract, Sodium Benzoate, Garden Cress (Lepidium Sativum) Sprout Extract

Other Information

Protect this product from excessive heat and direct sunlight

Distributed by: WELLNESS FOR LIFE PLLP

Anacortes, WA 99221

Wellness For Life Stay Ageless Daily Moisturizing Sunscreen Broad Spectrum SPF 25 1.7 fl oz (50 ml)

Wellness For Life
Stay Ageless Daily Moisturizing
Sunscreen Broad Spectrum SPF 25
1.7 fl oz (50 ml)